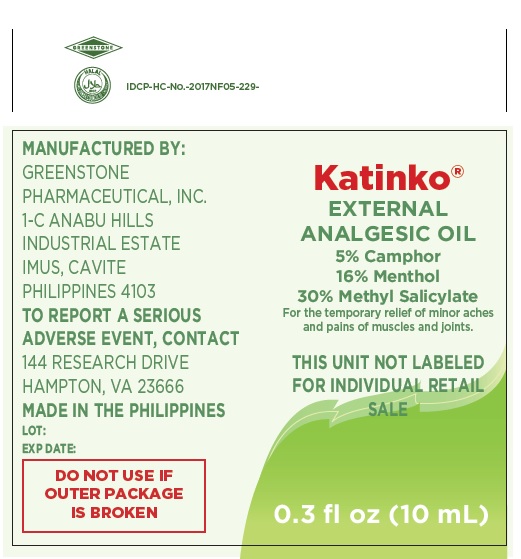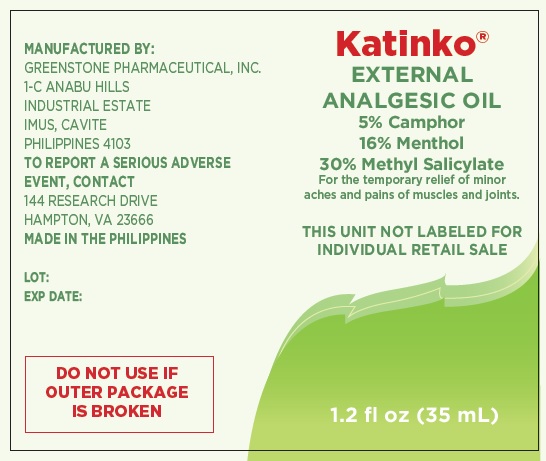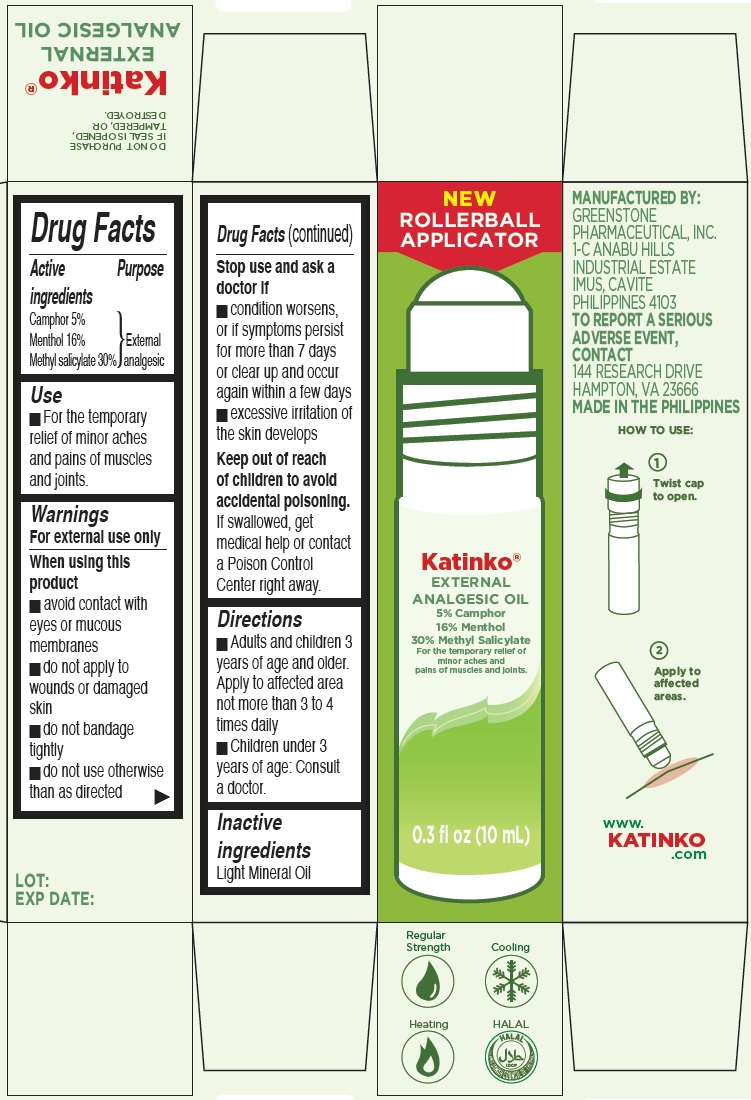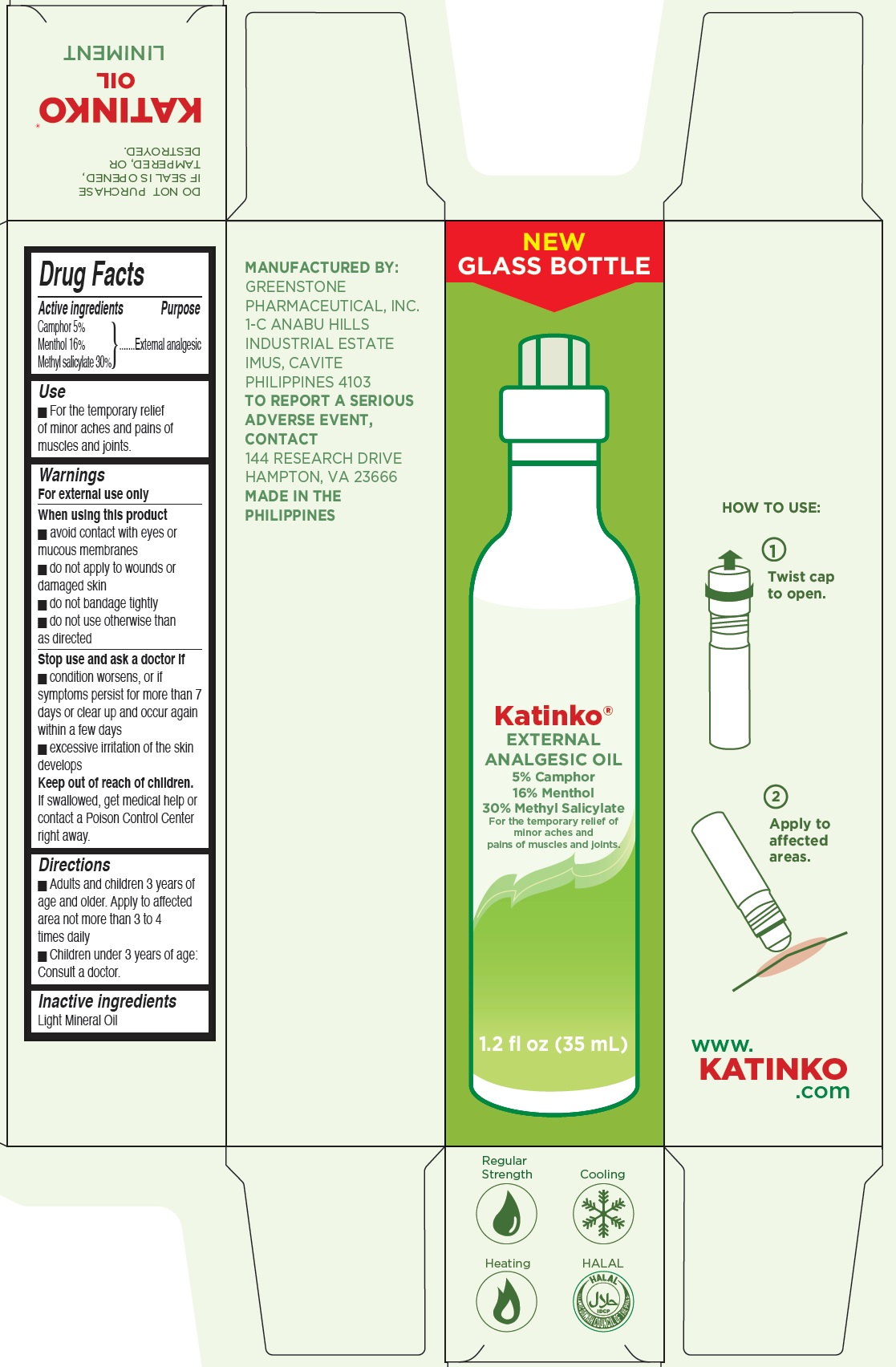 DRUG LABEL: Katinko External Analgesic Oil
NDC: 52241-301 | Form: OIL
Manufacturer: Greenstone Pharmaceutical Inc.
Category: otc | Type: HUMAN OTC DRUG LABEL
Date: 20231208

ACTIVE INGREDIENTS: CAMPHOR (SYNTHETIC) 50 mg/1 mL; MENTHOL 160 mg/1 mL; METHYL SALICYLATE 300 mg/1 mL
INACTIVE INGREDIENTS: MINERAL OIL

Katinko External Analgesic Oil

Active ingredients

Camphor 5% Menthol 16%

Methyl salicylate 30%

Purpose

External analgesic

Use

- For the temporary relief of minor aches and pains of muscles and joints.

Warnings

For external use only

When using this product

- avoid contact with eyes or mucous membranes
- do not apply to wounds or damaged skin
- do not bandage tightly
- do not use otherwise than as directed

Stop use and ask a doctor if

- condition worsens, or if symptoms persist for more than 7 days or clear up and occur again within a few days
- excessive irritation of the skin develops

Keep out of reach of children

If swallowed, get medical help or contact a Poison Control Center right away. to avoid accidental poisoning.

Directions

- Adults and children 3 years of age and older. Apply to affected area not more than 3 to 4 times daily
- Children under 3 years of age: Consult a doctor.

Inactive ingredients

Light Mineral Oil